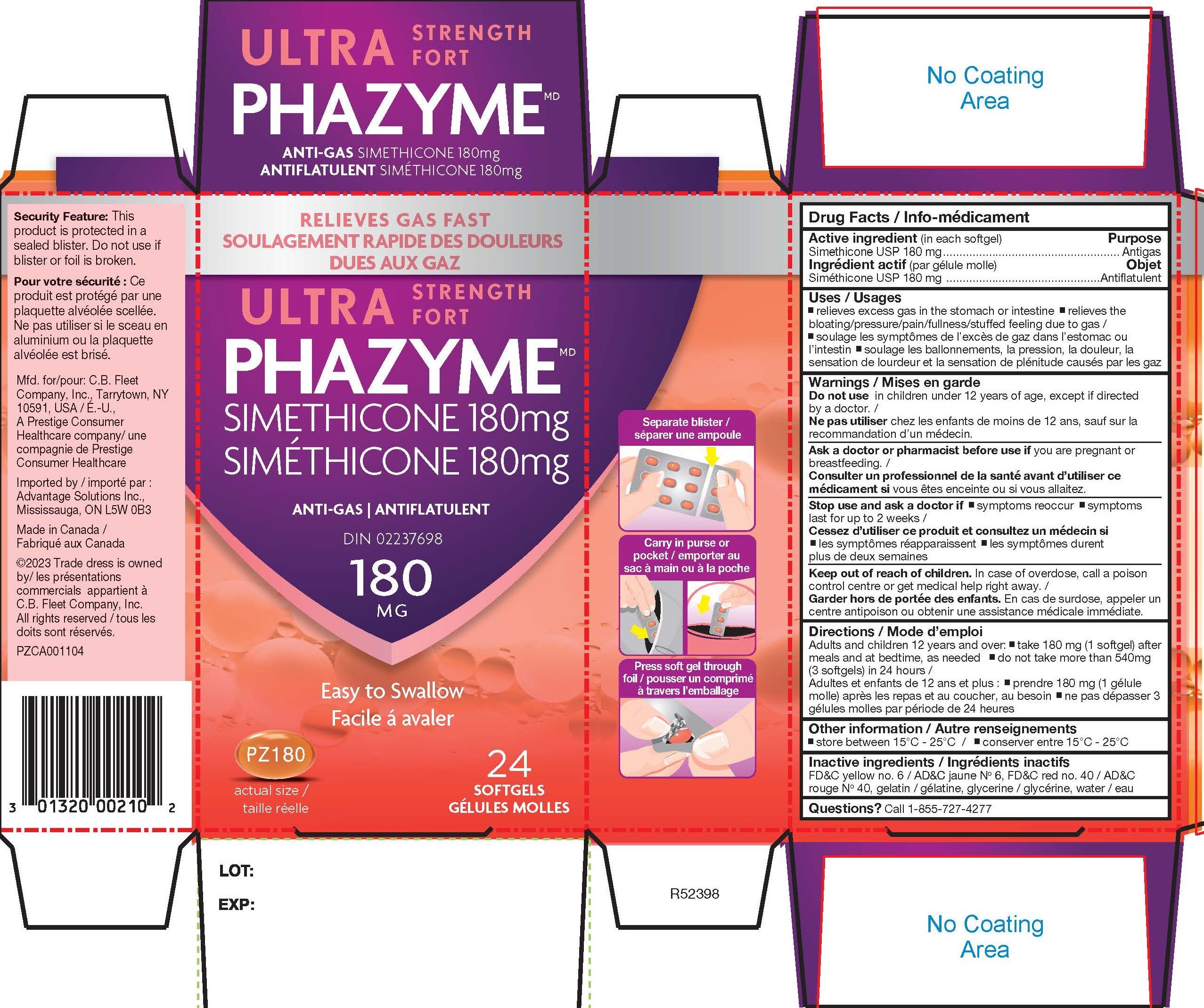 DRUG LABEL: Simethicone
NDC: 10267-5328 | Form: CAPSULE, LIQUID FILLED
Manufacturer: Contract Pharmacal Corp.
Category: otc | Type: HUMAN OTC DRUG LABEL
Date: 20240209

ACTIVE INGREDIENTS: DIMETHICONE 410 180 mg/1 1
INACTIVE INGREDIENTS: GLYCERIN; FD&C RED NO. 40; GELATIN; FD&C YELLOW NO. 6

5328- Export